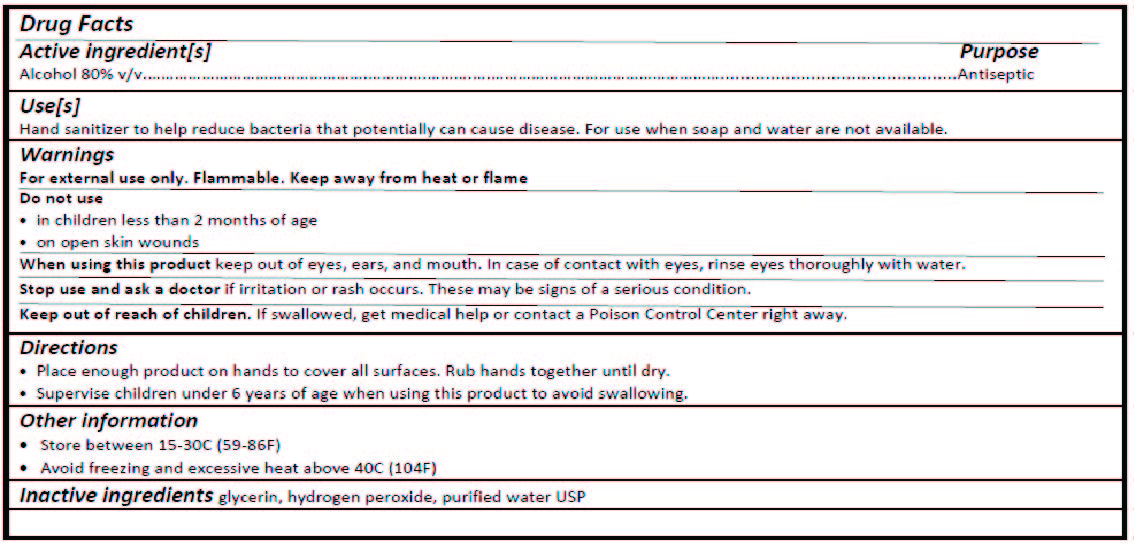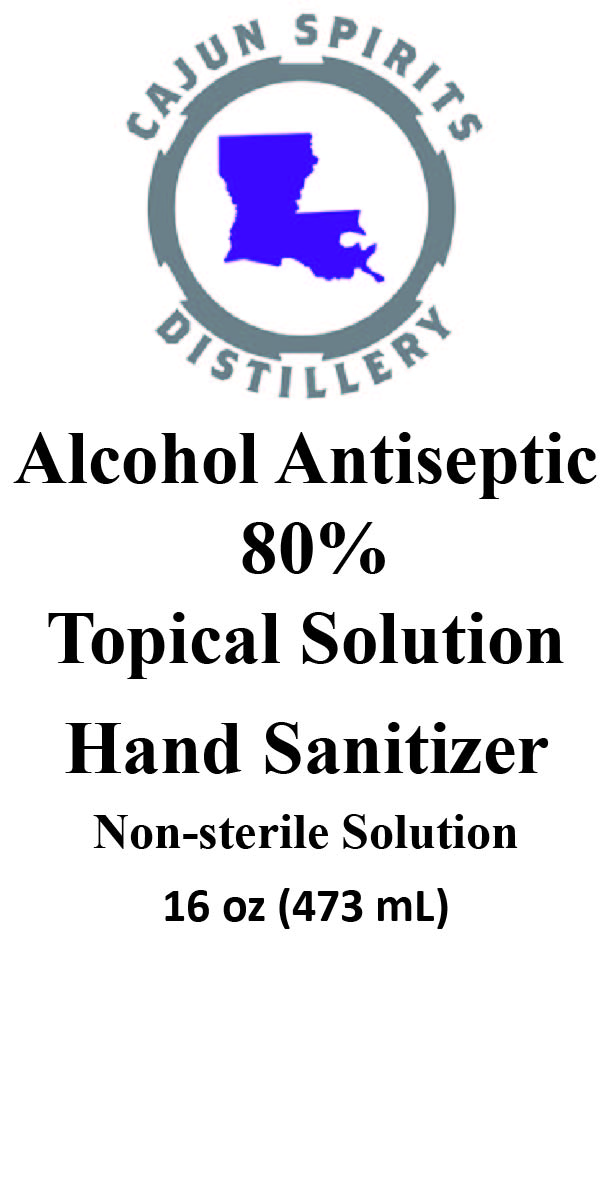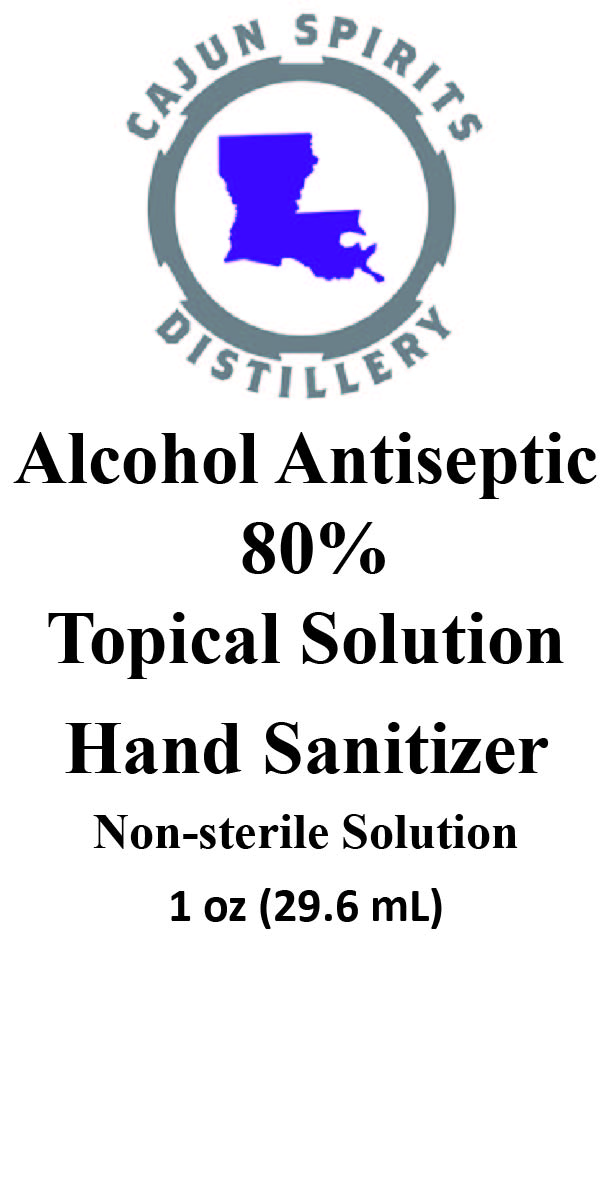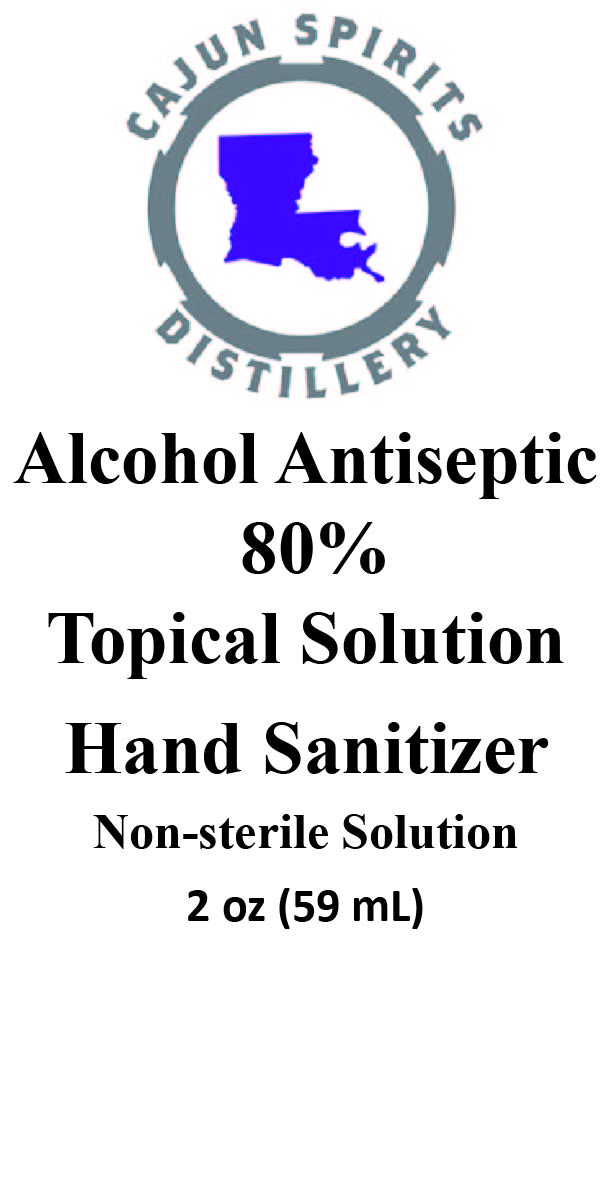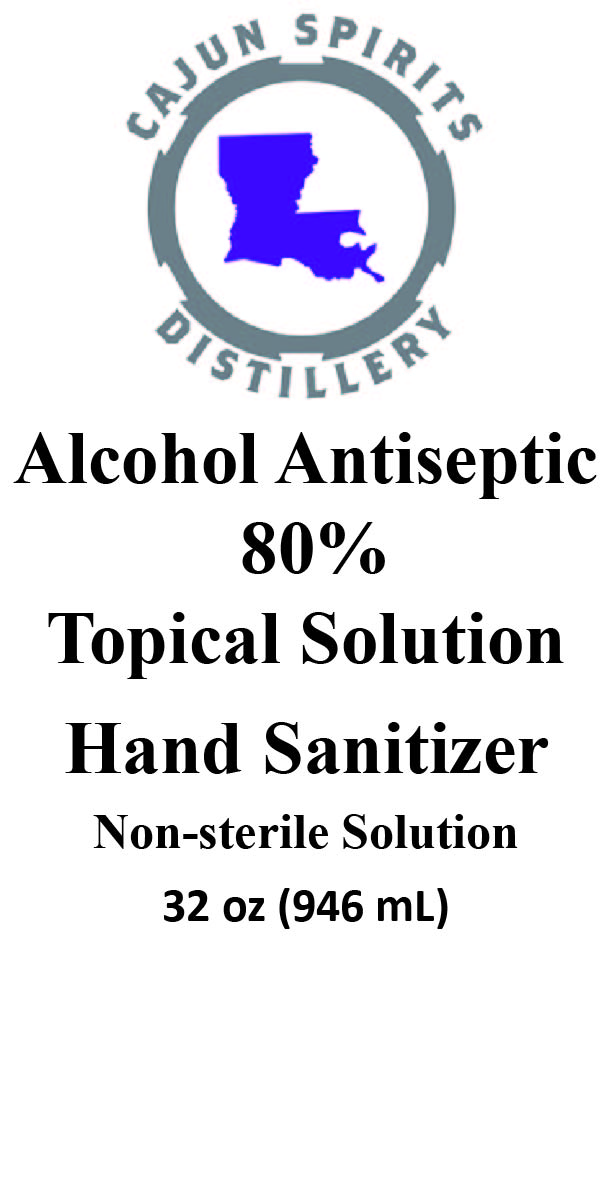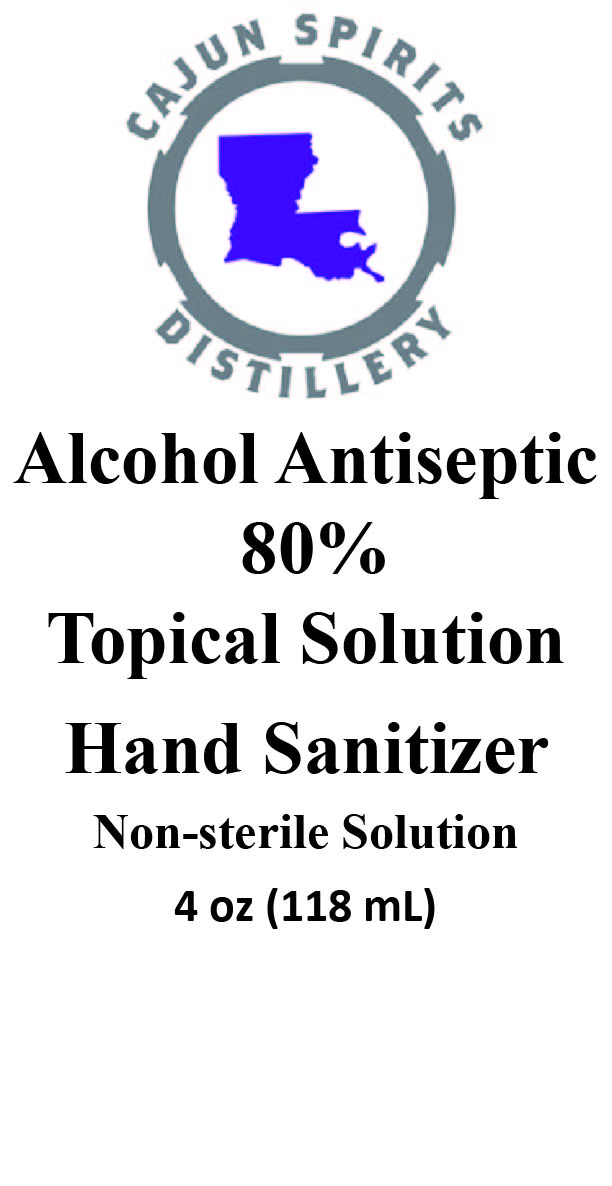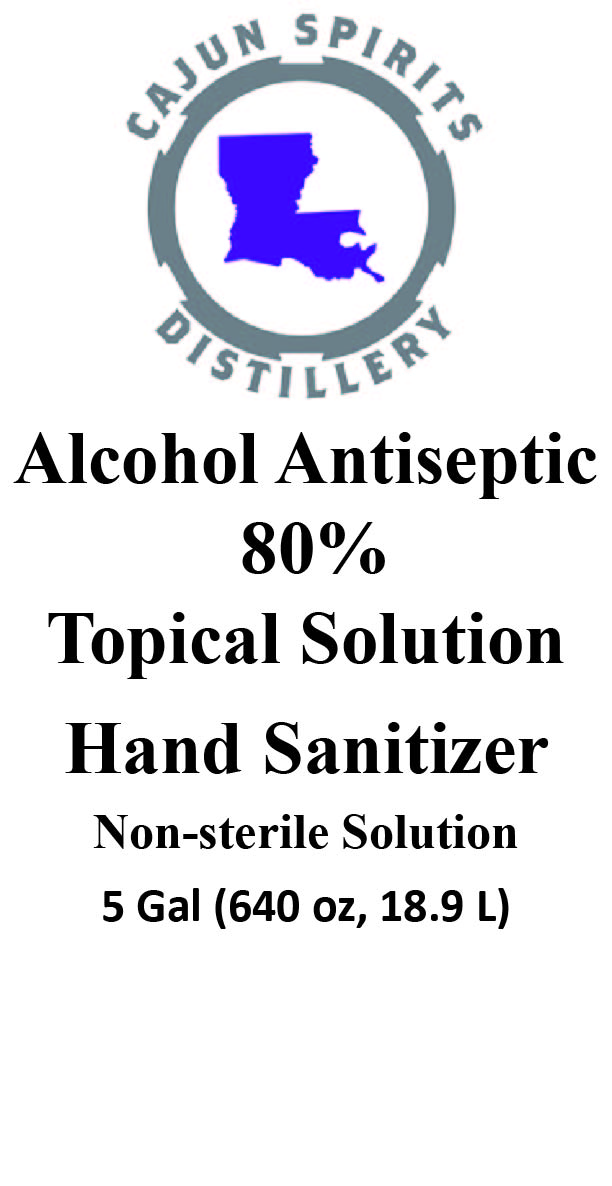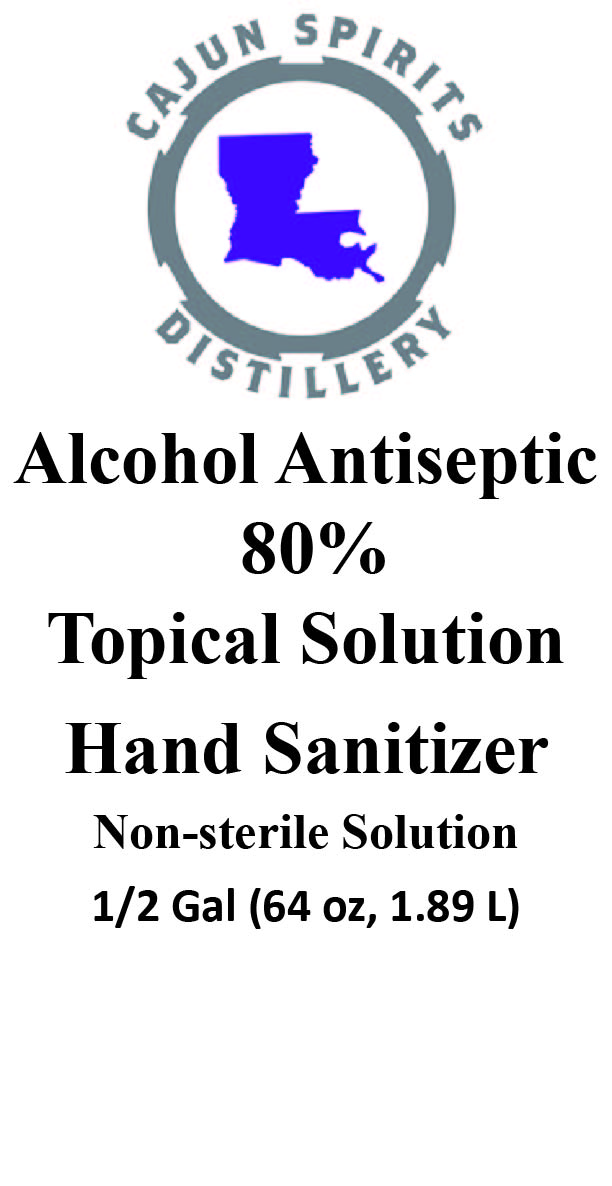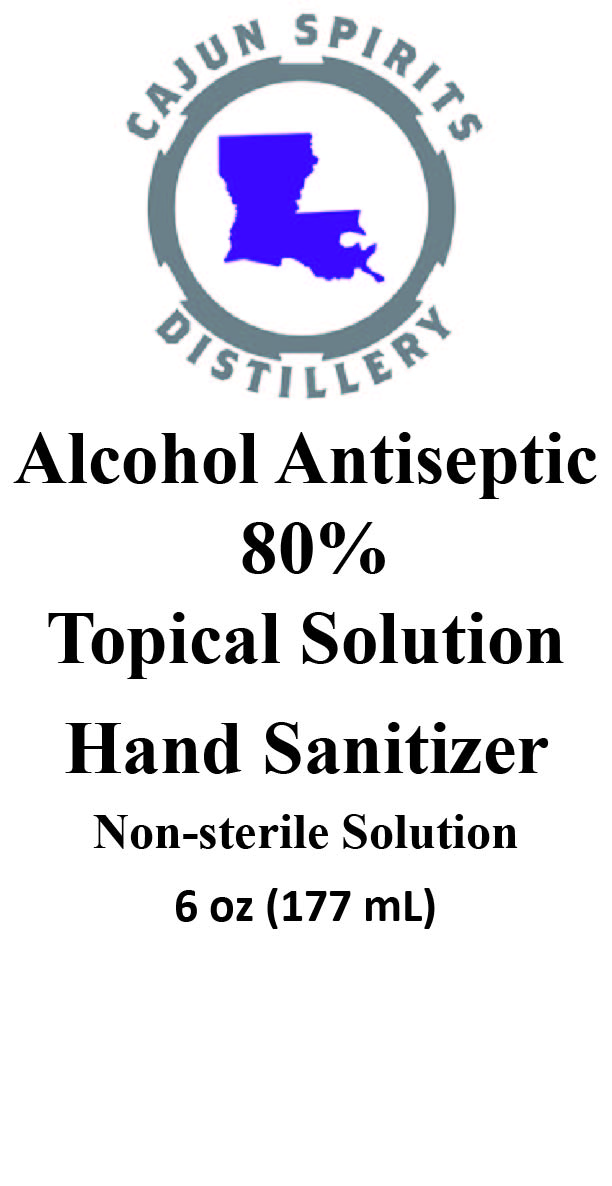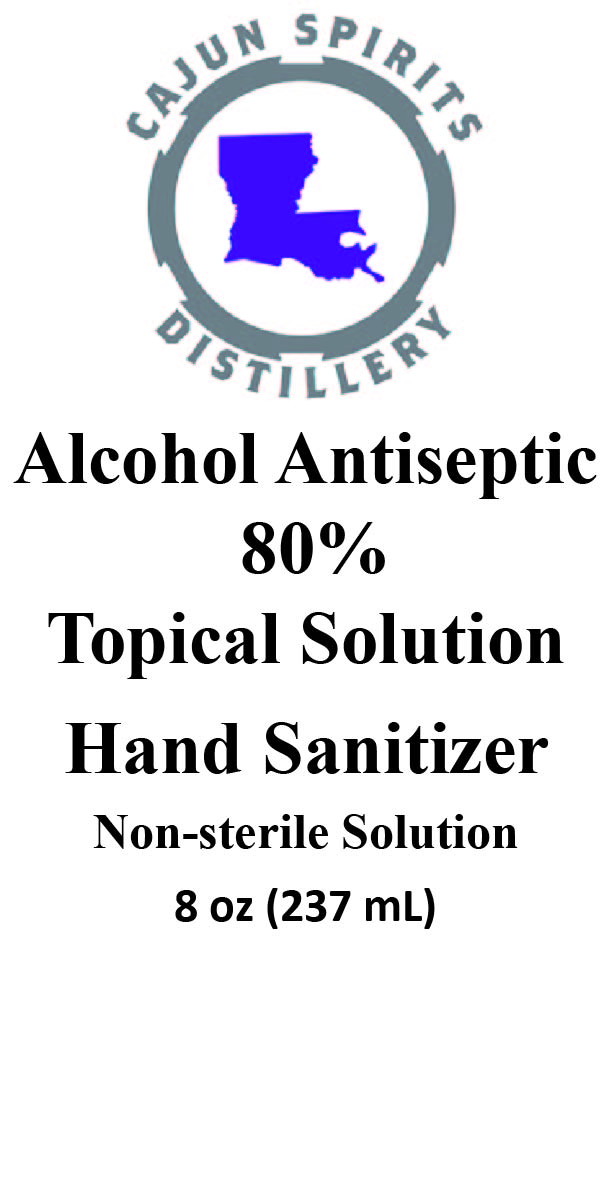 DRUG LABEL: Cajun Spirits Hand Sanitizer
NDC: 74152-001 | Form: LIQUID
Manufacturer: Cajun Spirits Distillery, LLC
Category: otc | Type: HUMAN OTC DRUG LABEL
Date: 20200327

ACTIVE INGREDIENTS: ALCOHOL 23.659 mL/29.574 mL
INACTIVE INGREDIENTS: HYDROGEN PEROXIDE 0.037 mL/29.574 mL; WATER 5.449 mL/29.574 mL; GLYCEROL FORMAL 0.429 mL/29.574 mL

Active Ingredients[s].

Alcohol 80%v/

Purpose

Anticeptic

Use

Hand sanitizer to help reduce bacteria that potentially can cause disease. For use when soap and water are not available.

Warnings

For external use only. Flammable. Keep away from heat or flame

Do not use

• in children less than 2 months of age

• on open skin wounds

When using this product

keep out of eyes, ears, and mouth. In case of contact with eyes, rinse eyes thoroughly with water.

Stop use and ask a doctor

if irritation or rash occurs. These may be signs of a serious condition.

Keep out of reach of children

If swallowed, get medical help or contact a Poison Control Center right away.

Directions

• Place enough product on hands to cover all surfaces. Rub hands together until dry.

• Supervise children under 6 years of age when using this product to avoid swallowing.

Other Information

• Store between 15-30C (59-86F)

• Avoid freezing and excessive heat above 40C (104F)

Inactive Ingredients

glycerin, hydrogen peroxide, purified water USP